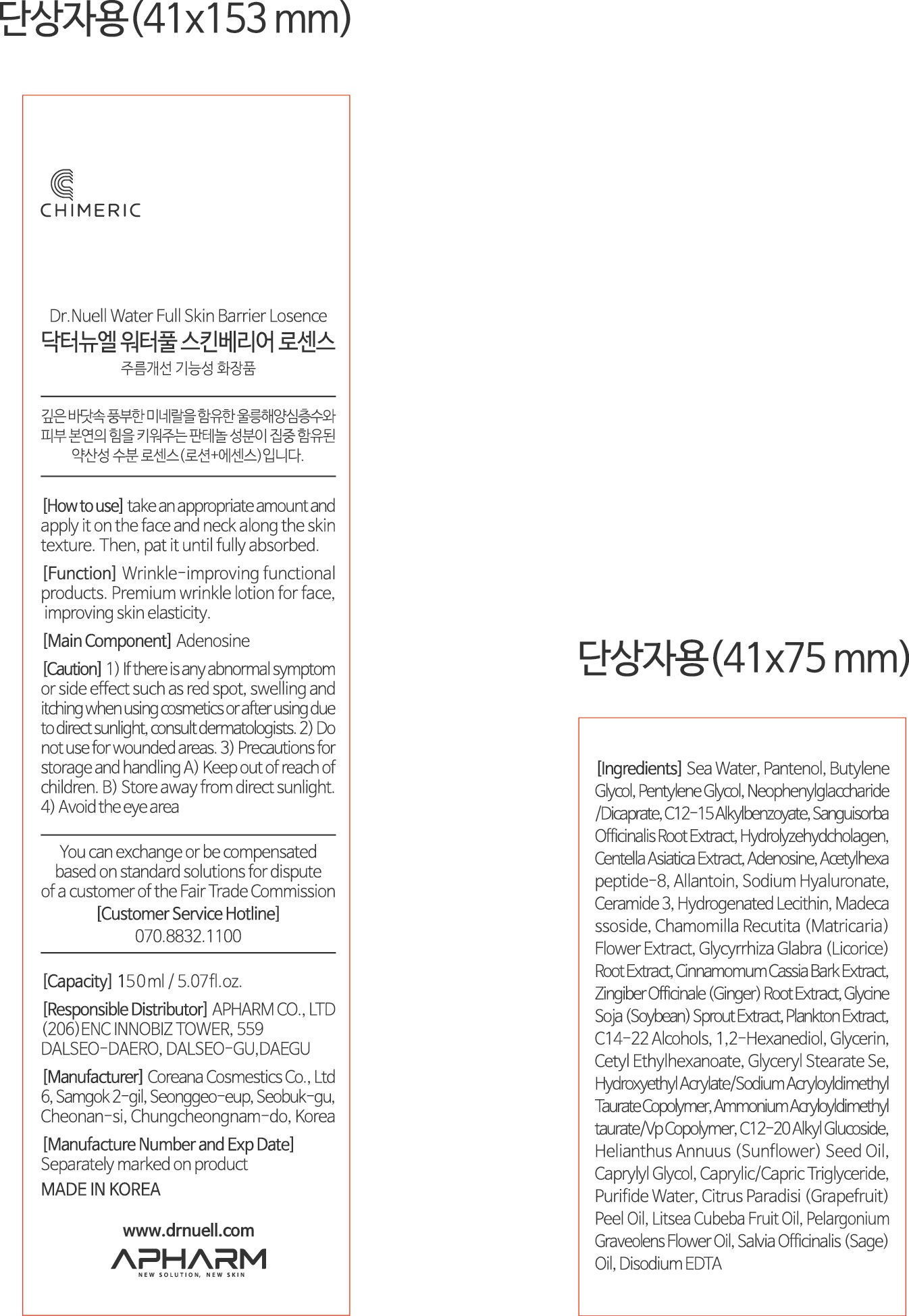 DRUG LABEL: Dr.NUELL Water Full Skin Barrier Losesnce
NDC: 73430-0006 | Form: CREAM
Manufacturer: Apharm Co., Ltd.
Category: otc | Type: HUMAN OTC DRUG LABEL
Date: 20191103

ACTIVE INGREDIENTS: GLYCERIN 0.59095 g/100 mL; ADENOSINE 0.04 g/100 mL
INACTIVE INGREDIENTS: ALLANTOIN; BUTYLENE GLYCOL

ACTIVE INGREDIENT

glycerin, adenosine

PURPOSE

wrinkle improving functional products.

premium wrinkle lotion for face, improving skin elasticity

Keep out of reach of children

INDICATIONS AND USAGE

take an appropriate amount and apply it on the face and neck along the skin texture, then, pat it until fully absorbed

WARNINGS

1) if there is any abnormal symptom or side effect, such as red spot, swelling and itching when using cosmetlcs or after using due to direct sunlight, consult dermatologists
2) Do not use for wounded areas
3) Precautions for storage and handling
keep out of reach of children, store away from direct sunlight
4) avoid the eye area

INACTIVE INGREDIENT

SEA WATER
PANTHENOL
BUTYLENE GLYCOL
PENTYLENE GLYCOL
NEOPENTYL GLYCOL DICAPRYLATE/DICAPRATE
C12-15 ALKYL BENZOATE
SANGUISORBA OFFICINALIS ROOT EXTRACT
HYDROLYZED COLLAGEN
CENTELLA ASIATICA EXTRACT
ACETYL HEXAPEPTIDE-8
ALLANTOIN
SODIUM HYALURONATE
CERAMIDE 3
HYDROGENATED LECITHIN
MADECASSOSIDE
CHAMOMILLA RECUTITA (MATRICARIA) FLOWER EXTRACT
GLYCYRRHIZA GLABRA (LICORICE) ROOT EXTRACT
CINNAMOMUM CASSIA BARK EXTRACT
ZINGIBER OFFICINALE (GINGER) ROOT EXTRACT
GLYCINE SOJA (SOYBEAN) SPROUT EXTRACT
PLANKTON EXTRACT
C14-22 ALCOHOLS
1,2-HEXANEDIOL
CETYL ETHYLHEXANOATE
GLYCERYL STEARATE SE
HYDROXYETHYL ACRYLATE/SODIUM ACRYLOYLDIMETHYL TAURATE COPOLYMER
AMMONIUM ACRYLOYLDIMETHYLTAURATE/VP COPOLYMER
C12-20 ALKYL GLUCOSIDE
HELIANTHUS ANNUUS (SUNFLOWER) SEED OIL
CAPRYLYL GLYCOL
CAPRYLIC/CAPRIC TRIGLYCERIDE
WATER
CITRUS PARADISI (GRAPEFRUIT) PEEL OIL
LITSEA CUBEBA FRUIT OIL
PELARGONIUM GRAVEOLENS FLOWER OIL
SALVIA OFFICINALIS (SAGE) OIL
DISODIUM EDTA

DOSAGE AND ADMINISTRATION

For external use only